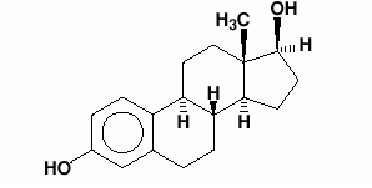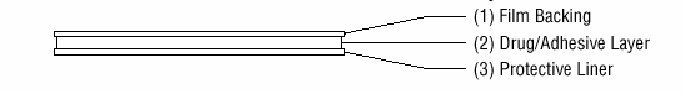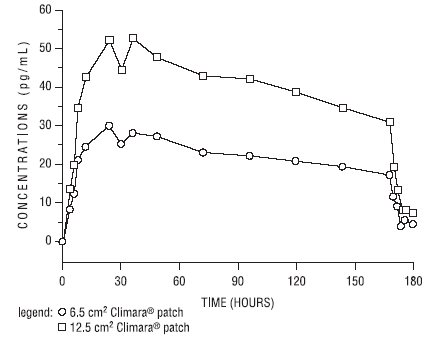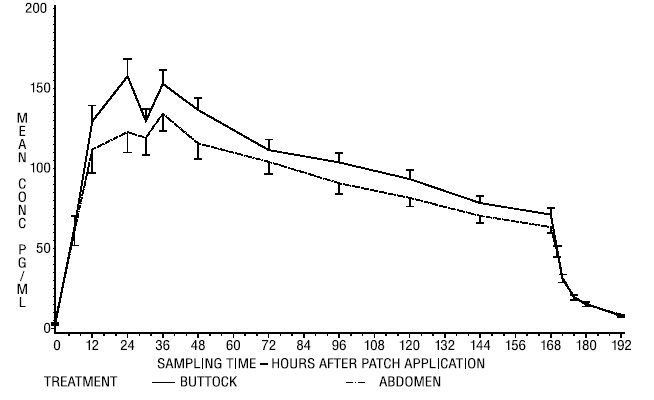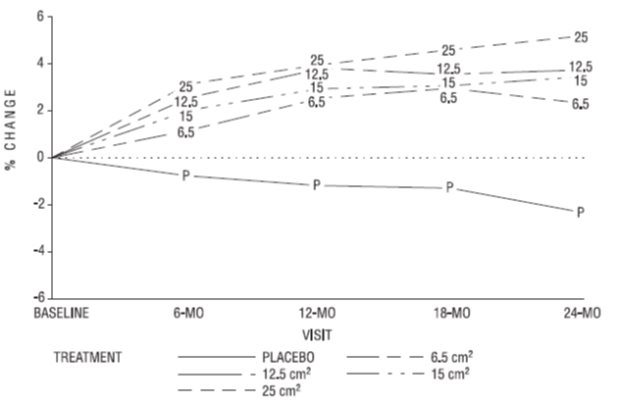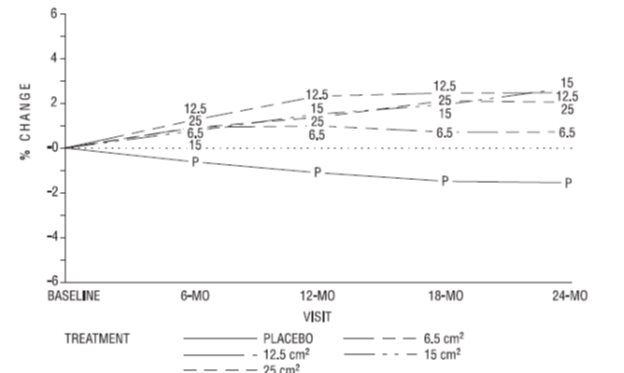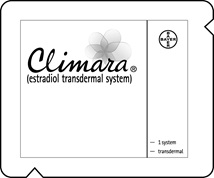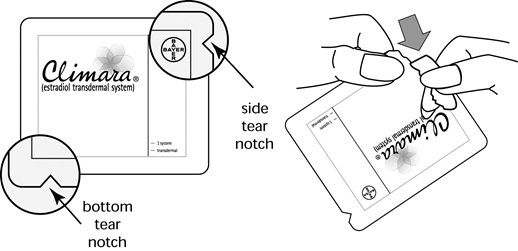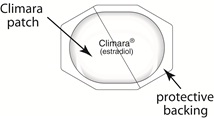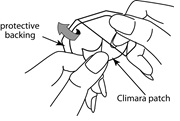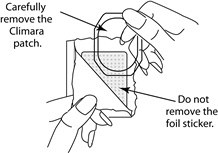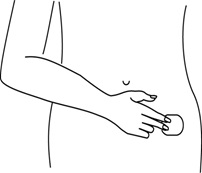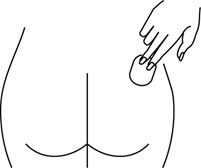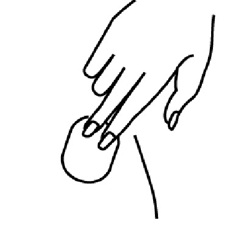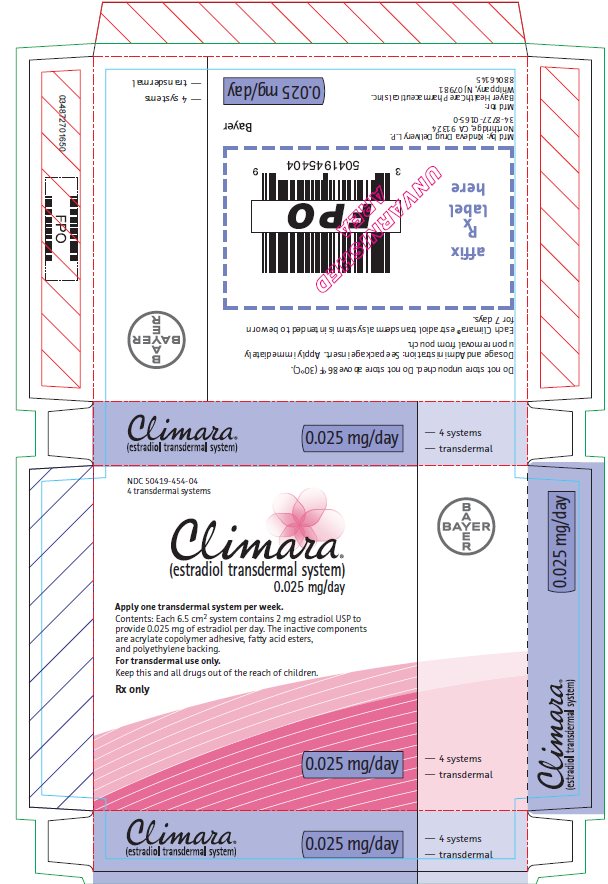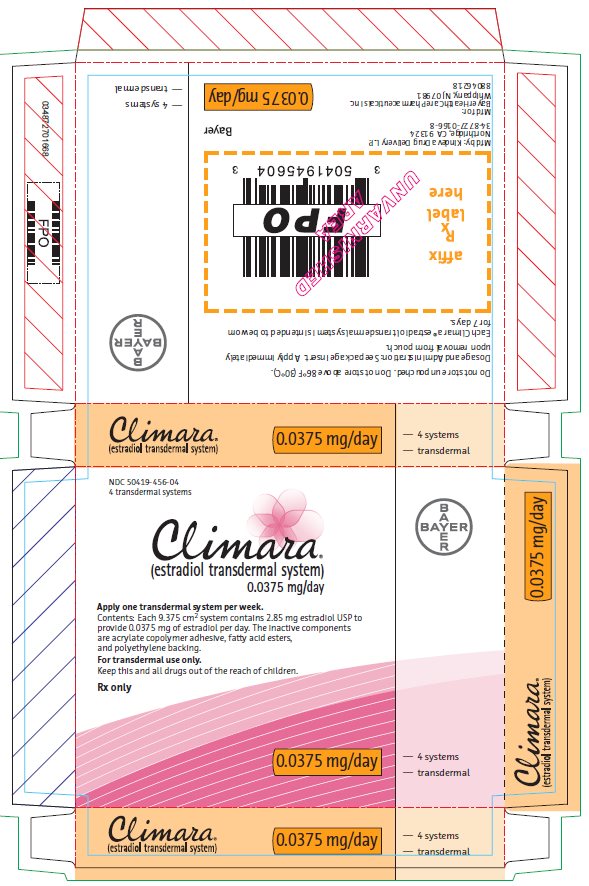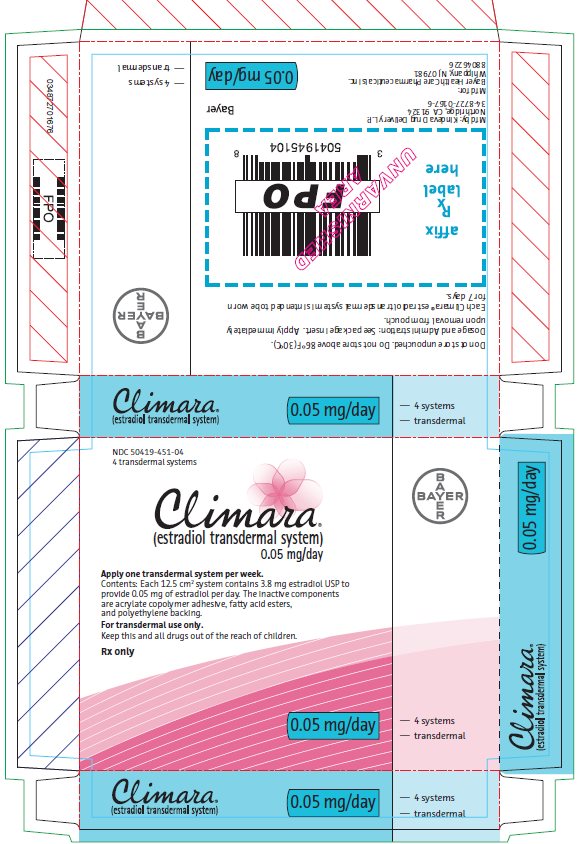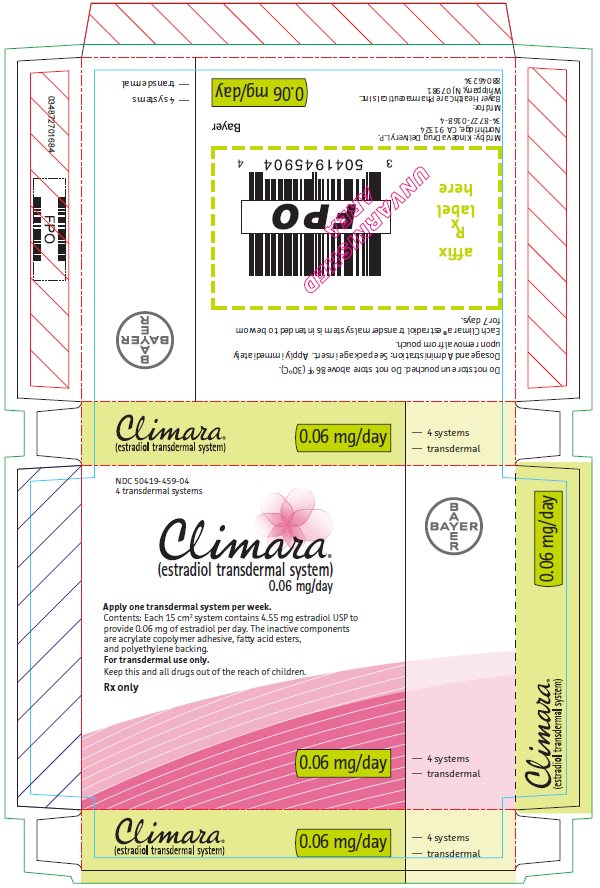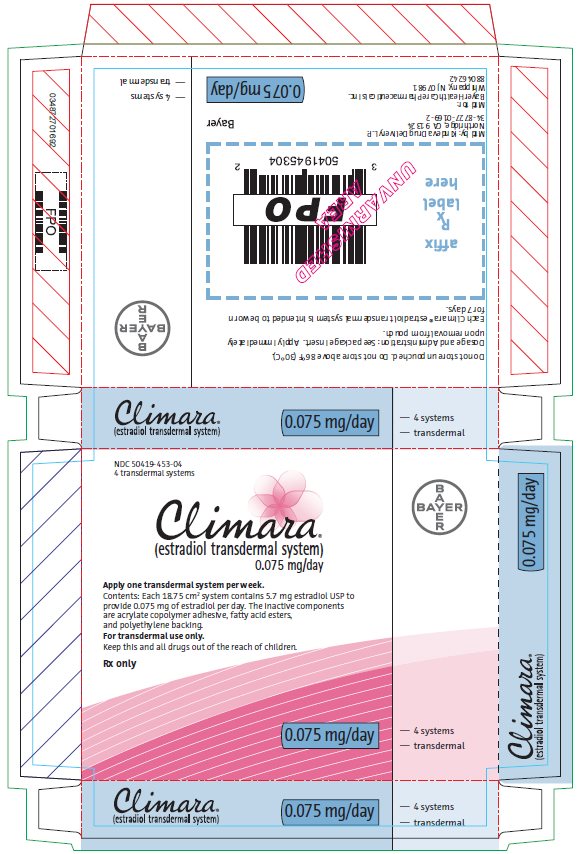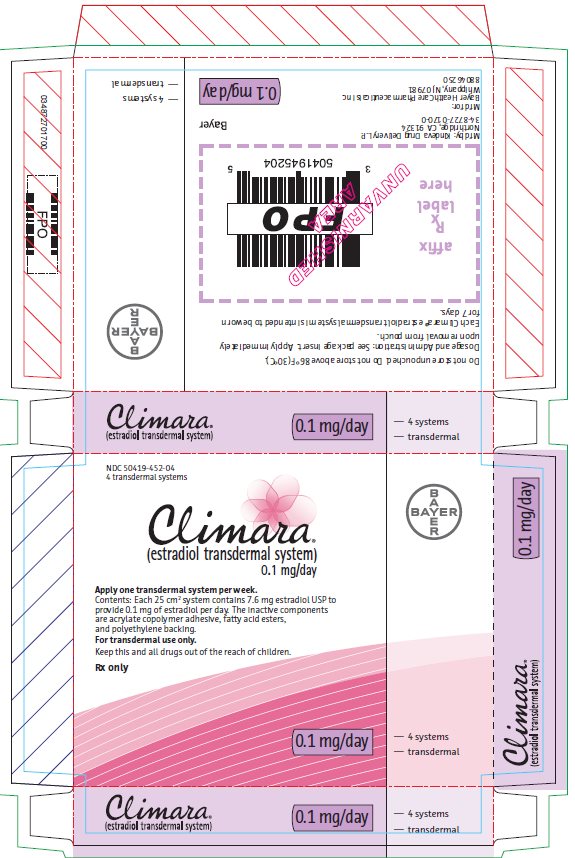 DRUG LABEL: Climara
NDC: 50419-454 | Form: PATCH
Manufacturer: Bayer HealthCare Pharmaceuticals Inc.
Category: prescription | Type: HUMAN PRESCRIPTION DRUG LABEL
Date: 20231206

ACTIVE INGREDIENTS: ESTRADIOL 0.025 mg/1 d

HIGHLIGHTS OF PRESCRIBING INFORMATION

These highlights do not include all the information needed to use CLIMARA safely and effectively. See full prescribing information for CLIMARA.
Climara® (estradiol transdermal system)
Initial U.S. Approval: 1975

RECENT MAJOR CHANGES

Warnings and Precautions (5.2) 12/2023

WARNING: ENDOMETRIAL CANCER, CARDIOVASCULAR DISORDERS, PROBABLE DEMENTIA and BREAST CANCER

See full prescribing information for complete boxed warning.

Estrogen-Alone Therapy

- There is an increased risk of endometrial cancer in a woman with a uterus who uses unopposed estrogens (5.2)
- The Women’s Health Initiative (WHI) estrogen-alone substudy reported increased risks of stroke and deep vein thrombosis (DVT) (5.1)
- The WHI Memory Study (WHIMS) estrogen-alone ancillary study of WHI reported an increased risk of probable dementia in postmenopausal women 65 years of age and older (5.3)
- Do not use estrogen-alone therapy for the prevention of cardiovascular disease or dementia (5.1, 5.3)

Estrogen Plus Progestin Therapy

- The WHI estrogen plus progestin substudy reported increased risks of stroke, DVT, pulmonary embolism (PE), and myocardial infarction (MI) (5.1)
- The WHI estrogen plus progestin substudy reported increased risks of invasive breast cancer (5.2)
- The WHIMS estrogen plus progestin ancillary study of WHI reported an increased risk of probable dementia in postmenopausal women 65 years of age and older (5.3)
- Do not use estrogen plus progestogen therapy for the prevention of cardiovascular disease or dementia (5.1, 5.3)

1 INDICATIONS AND USAGE

Climara is an estrogen indicated for:

- Treatment of Moderate to Severe Vasomotor Symptoms due to Menopause (1.1)
- Treatment of Moderate to Severe Symptoms of Vulvar and Vaginal Atrophy due to Menopause (1.2)
  Limitations of Use
  When prescribing solely for the treatment of moderate to severe symptoms of vulvar and vaginal atrophy due to menopause, first consider the use of topical vaginal products.
- Treatment of Hypoestrogenism due to Hypogonadism, Castration or Primary Ovarian Failure (1.3)
- Prevention of Postmenopausal Osteoporosis (1.4)
  Limitations of Use
  When prescribing solely for the prevention of postmenopausal osteoporosis, first consider the use of non-estrogen medications. Consider estrogen therapy only for women at significant risk of osteoporosis.

2 DOSAGE AND ADMINISTRATION

- Start therapy with Climara 0.025 mg per day applied to the skin once-weekly. Dosage adjustment should be guided by the clinical response (2.1)
- Place Climara on a clean, dry area of the lower abdomen (below the umbilicus) or upper quadrant of the buttock. Do not apply Climara to the breasts (2.5)

3 DOSAGE FORMS AND STRENGTHS

- Transdermal system 0.025 mg per day, 0.0375 mg per day, 0.05 mg per day, 0.06 mg per day, 0.075 mg per day and 0.1 mg per day (3)

4 CONTRAINDICATIONS

- Undiagnosed abnormal genital bleeding (4, 5.2)
- Breast cancer or a history of breast cancer (4, 5.2)
- Estrogen-dependent neoplasia (4, 5.2)
- Active DVT, PE or a history of these conditions (4, 5.1)
- Active arterial thromboembolic disease (for example, stroke or MI), or a history of these conditions (4, 5.1)
- Known anaphylactic reaction, or angioedema, or hypersensitivity to Climara (4)
- Hepatic impairment or disease (4, 5.10)
- Protein C, protein S, or antithrombin deficiency, or other known thrombophilic disorders (4)

5 WARNINGS AND PRECAUTIONS

- Estrogens increase the risk of gallbladder disease (5.4)
- Discontinue estrogen if severe hypercalcemia, loss of vision, severe hypertriglyceridemia or cholestatic jaundice occurs (5.5, 5.6, 5.9, 5.10)
- Monitor thyroid function in women on thyroid hormone replacement therapy (5.11, 5.18)

6 ADVERSE REACTIONS

The most common adverse reactions (≥10 percent) with Climara are: breast pain, upper respiratory tract infections, headaches, abdominal pain, pain, and edema. (6.1)

To report SUSPECTED ADVERSE REACTIONS, contact Bayer HealthCare Pharmaceuticals Inc. at 1-888-84-BAYER (1-888-842-2937) or FDA at 1-800-FDA-1088 or www.fda.gov/medwatch.

7 DRUG INTERACTIONS

  - Inducers and/or inhibitors of CYP3A4 may affect estrogen drug metabolism and decrease or increase the estrogen plasma concentration. (7)

FULL PRESCRIBING INFORMATION

WARNING: ENDOMETRIAL CANCER, CARDIOVASCULAR DISORDERS, PROBABLE DEMENTIA and BREAST CANCER

Estrogen-Alone Therapy

Endometrial Cancer

There is an increased risk of endometrial cancer in a woman with a uterus who uses unopposed estrogens. Adding a progestogen to estrogen therapy has been shown to reduce the risk of endometrial hyperplasia, which may be a precursor to endometrial cancer. Perform adequate diagnostic measures, including directed or random endometrial sampling when indicated to rule out malignancy in postmenopausal women with undiagnosed, persistent or recurring abnormal genital bleeding [see Warnings and Precautions (5.2)].

Cardiovascular Disorders and Probable Dementia

The Women’s Health Initiative (WHI) estrogen-alone substudy reported increased risks of stroke and deep vein thrombosis (DVT) in postmenopausal women (50 to 79 years of age) during 7.1 years of treatment with daily oral conjugated estrogens (CE) [0.625 mg]-alone, relative to placebo [see Warnings and Precautions (5.1), and Clinical Studies (14.3)].

The WHI Memory Study (WHIMS) estrogen-alone ancillary study of the WHI reported an increased risk of developing probable dementia in postmenopausal women 65 years of age and older during 5.2 years of treatment with daily CE (0.625 mg)-alone, relative to placebo. It is unknown whether this finding applies to younger postmenopausal women [see Warnings and Precautions (5.3), Use in Specific Populations (8.5), and Clinical Studies (14.4)].

Do not use estrogen-alone therapy for the prevention of cardiovascular disease or dementia [see Warnings and Precautions (5.1, 5.3), and Clinical Studies (14.3, 14.4)].

Only daily oral 0.625 mg CE was studied in the estrogen-alone substudy of the WHI. Therefore, the relevance of the WHI findings regarding adverse cardiovascular events and dementia to lower CE doses, other routes of administration, or other estrogen-alone products is not known. Without such data, it is not possible to definitively exclude these risks or determine the extent of these risks for other products. Discuss with your patient the benefits and risks of estrogen-alone therapy, taking into account her individual risk profile.

Prescribe estrogens with or without progestogens at the lowest effective doses and for the shortest duration consistent with treatment goals and risks for the individual woman.

Estrogen Plus Progestin Therapy

Cardiovascular Disorders and Probable Dementia

The WHI estrogen plus progestin substudy reported increased risks of DVT, pulmonary embolism (PE), stroke and myocardial infarction (MI) in postmenopausal women (50 to 79 years of age) during 5.6 years of treatment with daily oral CE (0.625 mg) combined with medroxyprogesterone acetate (MPA) [2.5 mg], relative to placebo [see Warnings and Precautions (5.1), and Clinical Studies (14.3)].

The WHIMS estrogen plus progestin ancillary study of the WHI reported an increased risk of developing probable dementia in postmenopausal women 65 years of age and older during 4 years of treatment with daily CE (0.625 mg) combined with MPA (2.5 mg), relative to placebo. It is unknown whether this finding applies to younger postmenopausal women [see Warnings and Precautions (5.3), Use in Specific Populations (8.5), and Clinical Studies (14.4)].

Do not use estrogen plus progestogen therapy for the prevention of cardiovascular disease or dementia [see Warnings and Precautions (5.1, 5.3), and Clinical Studies (14.3, 14.4)].

Breast Cancer

The WHI estrogen plus progestin substudy also demonstrated an increased risk of invasive breast cancer [see Warnings and Precautions (5.2), and Clinical Studies (14.3)].

Only daily oral 0.625 mg CE and 2.5 mg MPA were studied in the estrogen plus progestin substudy of the WHI. Therefore, the relevance of the WHI findings regarding adverse cardiovascular events, dementia and breast cancer to lower CE plus other MPA doses, other routes of administration, or other estrogen plus progestogen products is not known. Without such data, it is not possible to definitively exclude these risks or determine the extent of these risks for other products. Discuss with your patient the benefits and risks of estrogen plus progestogen therapy, taking into account her individual risk profile.

Prescribe estrogens with or without progestogens at the lowest effective doses and for the shortest duration consistent with treatment goals and risks for the individual woman.

1 INDICATIONS AND USAGE

1.2 Treatment of Moderate to Severe Symptoms of Vulvar and Vaginal Atrophy due to Menopause

Limitation of Use

When prescribing solely for the treatment of moderate to severe symptoms of vulvar and vaginal atrophy due to menopause, first consider the use of topical vaginal products.

1.4 Prevention of Postmenopausal Osteoporosis

Limitation of Use

When prescribing solely for the prevention of postmenopausal osteoporosis, first consider the use of non-estrogen medications. Consider estrogen therapy only for women at significant risk of osteoporosis

2 DOSAGE AND ADMINISTRATION

Generally, when estrogen is prescribed for a postmenopausal woman with a uterus, consider addition of a progestogen to reduce the risk of endometrial cancer. Generally, a woman without a uterus does not need to use a progestogen in addition to her estrogen therapy. In some cases, however, hysterectomized women who have a history of endometriosis may need a progestogen [see Warnings and Precautions (5.2, 5.14)].

Use estrogen-alone, or in combination with a progestogen at the lowest effective dose and for the shortest duration consistent with treatment goals and risks for the individual woman. Reevaluate postmenopausal women periodically as clinically appropriate to determine if treatment is still necessary.

2.1 Treatment of Moderate to Severe Vasomotor Symptoms due to Menopause

Start therapy with Climara 0.025 mg per day applied to the skin once weekly. Make dosage adjustments based on the clinical response. Attempt to taper or discontinue Climara at 3 to 6 month intervals.

2.2 Treatment of Moderate to Severe Symptoms of Vulvar and Vaginal Atrophy due to Menopause

Start therapy with Climara 0.025 mg per day applied to the skin once weekly. Make dosage adjustments based on the clinical response. Attempt to taper or discontinue Climara at 3 to 6 month intervals.

2.3 Treatment of Hypoestrogenism due to Hypogonadism, Castration, or Primary Ovarian Failure

Start therapy with 0.025 mg per day applied to the skin once weekly. Make dose adjustment based on the clinical response.

2.4 Prevention of Postmenopausal Osteoporosis

Start therapy with Climara 0.025 mg per day applied to the skin once weekly.

2.5 Application of the Climara Transdermal System

Site Selection

- Place the adhesive side of Climara on a clean, dry area of the lower abdomen or the upper quadrant of the buttock.
- Do not apply Climara to or near the breasts.
- Rotate the sites of application, with an interval of at least 1-week allowed between applications to the same site.
- Select an area that is not oily, damaged, or irritated. Avoid the waistline, since tight clothing may rub the transdermal system off.
- Avoid application to areas where sitting would dislodge Climara.

Application

- Apply Climara immediately after opening the pouch and removing the protective liner.
- Press Climara firmly in place with the fingers for at least 10 seconds, making sure there is good contact, especially around the edges.
- If the system lifts, apply pressure to maintain adhesion.
- In the event that a system falls off, reapply it to a different location. If the old system cannot be reapplied, apply a new system for the remainder of the 7-day dosing interval.
- Wear only one system at any one time during the 7-day dosing interval.
- Swimming, bathing, or using a sauna while using Climara has not been studied, and these activities may decrease the adhesion of the system and the delivery of estradiol.

2.6 Removal of the Climara Transdermal System

- Remove Climara carefully and slowly to avoid irritation of the skin.
- If any adhesive remains on the skin after removal of Climara, allow the area to dry for 15 minutes and then gently rub the area with an oil-based cream or lotion to remove the adhesive residue.
- Used patches still contain some active hormones. Carefully fold each patch in half so that it sticks to itself before throwing it away.

3 DOSAGE FORMS AND STRENGTHS

- Climara (estradiol transdermal system), 0.025 mg per day—each 6.5 cm^2 system contains 2 mg of estradiol
- Climara (estradiol transdermal system), 0.0375 mg per day—each 9.375 cm^2 system contains 2.85 mg of estradiol
- Climara (estradiol transdermal system), 0.05 mg per day—each 12.5 cm^2 system contains 3.8 mg of estradiol
- Climara (estradiol transdermal system), 0.060 mg per day—each 15 cm^2 system contains 4.55 mg of estradiol
- Climara (estradiol transdermal system), 0.075 mg per day—each 18.75 cm^2 system contains 5.7 mg of estradiol
- Climara (estradiol transdermal system), 0.1 mg per day—each 25.0 cm^2 system contains 7.6 mg of estradiol

4 CONTRAINDICATIONS

Climara is contraindicated in women with any of the following conditions:

- Undiagnosed abnormal genital bleeding [see Warnings and Precautions (5.2)]
- Breast cancer or history of breast cancer [see Warnings and Precautions (5.2)]
- Estrogen-dependent neoplasia [see Warnings and Precautions (5.2)]
- Active DVT, PE, or a history of these conditions [see Warnings and Precautions (5.1)]
- Active arterial thromboembolic disease (for example, stroke or MI), or a history of these conditions [see Warnings and Precautions (5.1)]
- Known anaphylactic reaction, or angioedema, or hypersensitivity to Climara
- Hepatic impairment or disease
- Protein C, protein S, or antithrombin deficiency, or other known thrombophilic disorders

5 WARNINGS AND PRECAUTIONS

5.1 Cardiovascular Disorders

Increased risks of stroke and DVT are reported with estrogen-alone therapy. Increased risks of PE, DVT, stroke and MI are reported with estrogen plus progestin therapy. Immediately discontinue estrogen with or without progestogen therapy if any of these occur or are suspected.

Manage appropriately any risk factors for arterial vascular disease (for example, hypertension, diabetes mellitus, tobacco use, hypercholesterolemia, and obesity) and/or venous thromboembolism (VTE) (for example, personal history or family history of VTE, obesity, and systemic lupus erythematosus).

Stroke

The WHI estrogen-alone substudy reported a statistically significant increased risk of stroke in women 50 to 79 years of age receiving daily CE (0.625 mg)-alone compared to women in the same age group receiving placebo (45 versus 33 strokes per 10,000 women-years, respectively). The increase in risk was demonstrated in year 1 and persisted [see Clinical Studies (14.3)]. Immediately discontinue estrogen-alone therapy if a stroke occurs or is suspected.

Subgroup analyses of women 50 to 59 years of age suggest no increased risk of stroke for those women receiving CE (0.625 mg)-alone versus those receiving placebo (18 versus 21 per 10,000 women-years).^1

The WHI estrogen plus progestin substudy reported a statistically significant increased risk of stroke in women 50 to 79 years of age receiving daily CE (0.625 mg) plus MPA (2.5 mg) compared to women in the same age group receiving placebo (33 versus 25 strokes per 10,000 women years, respectively) [see Clinical Studies (14.3)]. The increase in risk was demonstrated after the first year and persisted.^1 Immediately discontinue estrogen plus progestogen therapy if a stroke occurs or is suspected.

Coronary Heart Disease

The WHI estrogen-alone substudy reported no overall effect on coronary heart disease (CHD) events (defined as nonfatal MI, silent MI, or CHD death) in women receiving estrogen-alone compared to placebo^2 [see Clinical Studies (14.3)].

Subgroup analyses of women 50 to 59 years of age, who were less than 10 years since menopause, suggest a reduction (not statistically significant) of CHD events in those women receiving daily CE (0.625 mg)-alone compared to placebo (8 versus 16 per 10,000 women-years).^1

The WHI estrogen plus progestin substudy reported an increased risk (not statistically significant) of CHD events in women receiving daily CE (0.625 mg) plus MPA (2.5 mg) compared to women receiving placebo (41 versus 34 per 10,000 women-years).^1 An increase in relative risk was demonstrated in year 1, and a trend toward decreasing relative risk was reported in years 2 through 5 [see Clinical Studies (14.3)].

In postmenopausal women with documented heart disease (n = 2,763), average 66.7 years of age, in a controlled clinical trial of secondary prevention of cardiovascular disease (Heart and Estrogen/Progestin Replacement Study; HERS), treatment with daily CE (0.625 mg) plus MPA (2.5 mg) demonstrated no cardiovascular benefit. During an average follow-up of 4.1 years, treatment with CE plus MPA did not reduce the overall rate of CHD events in postmenopausal women with established CHD. There were more CHD events in the CE plus MPA-treated group than in the placebo group in year 1, but not during the subsequent years. Two thousand three hundred twenty-one (2,321) women from the original HERS trial agreed to participate in an open label extension of HERS, HERS II. Average follow-up in HERS II was an additional 2.7 years, for a total of 6.8 years overall. Rates of CHD events were comparable among women in the CE plus MPA group and the placebo group in HERS, HERS II, and overall.

Venous Thromboembolism

In the WHI estrogen-alone substudy, the risk of VTE (DVT and PE) was increased for women receiving daily CE (0.625 mg)-alone compared to placebo (30 versus 22 per 10,000 women-years), although only the increased risk of DVT reached statistical significance (23 versus 15 per 10,000 women-years). The increase in VTE risk was demonstrated during the first 2 years^3 [see Clinical Studies (14.3)]. Immediately discontinue estrogen-alone therapy if a VTE occurs or is suspected.

The WHI estrogen plus progestin substudy reported a statistically significant 2-fold greater rate of VTE in women receiving daily CE (0.625 mg) plus MPA (2.5 mg) compared to women receiving placebo (35 versus 17 per 10,000 women-years). Statistically significant increases in risk for both DVT (26 versus 13 per 10,000 women-years) and PE (18 versus 8 per 10,000 women-years) were also demonstrated. The increase in VTE risk was demonstrated during the first year and persisted^4 [see Clinical Studies (14.3)]. Immediately discontinue estrogen plus progestogen therapy if a VTE occurs or is suspected.

If feasible, discontinue estrogens at least 4 to 6 weeks before surgery of the type associated with an increased risk of thromboembolism, or during periods of prolonged immobilization.

5.2 Malignant Neoplasms

Endometrial Cancer

An increased risk of endometrial cancer has been reported with the use of unopposed estrogen therapy in a woman with a uterus. The reported endometrial cancer risk among unopposed estrogen users is about 2 to 12 times greater than in non-users and appears dependent on duration of treatment and on estrogen dose. Most studies show no significant increased risk associated with use of estrogens for less than 1 year. The greatest risk appears associated with prolonged use, with increased risks of 15- to 24-fold for 5 to 10 years or more, and this risk has been shown to persist for at least 8 to 15 years after estrogen therapy is discontinued.

Clinical surveillance of all women using estrogen-alone or estrogen plus progestogen therapy is important. Perform adequate diagnostic measures, including directed or random endometrial sampling when indicated, to rule out malignancy in postmenopausal women with undiagnosed persistent or recurring abnormal genital bleeding with unknown etiology.

There is no evidence that the use of natural estrogens results in a different endometrial risk profile than synthetic estrogens of equivalent estrogen dose. Adding a progestogen to estrogen therapy in postmenopausal women has been shown to reduce the risk of endometrial hyperplasia, which may be a precursor to endometrial cancer.

Breast Cancer

The WHI substudy of daily CE (0.625 mg)-alone provided information about breast cancer in estrogen-alone users. In the WHI estrogen-alone substudy, after an average follow-up of 7.1 years, daily CE (0.625 mg)-alone was not associated with an increased risk of invasive breast cancer [relative risk (RR) 0.80]^5 [see Clinical Studies (14.3)].

After a mean follow-up of 5.6 years, the WHI substudy of daily CE (0.625 mg) plus MPA (2.5 mg) reported an increased risk of invasive breast cancer in women who took daily CE plus MPA compared to placebo.

In this substudy, prior use of estrogen-alone or estrogen plus progestin therapy was reported by 26 percent of the women. The relative risk of invasive breast cancer was 1.24, and the absolute risk was 41 versus 33 cases per 10,000 women-years, for CE plus MPA compared with placebo. Among women who reported prior use of hormone therapy, the relative risk of invasive breast cancer was 1.86, and the absolute risk was 46 versus 25 cases per 10,000 women-years for CE plus MPA compared with placebo.^6 Among women who reported no prior use of hormone therapy, the relative risk of invasive breast cancer was 1.09, and the absolute risk was 40 versus 36 cases per 10,000 women-years for CE plus MPA compared with placebo. In the same substudy, invasive breast cancers were larger, were more likely to be node positive, and were diagnosed at a more advanced stage in the CE (0.625 mg) plus MPA (2.5 mg) group compared with the placebo group. Metastatic disease was rare, with no apparent difference between the two groups. Other prognostic factors, such as histologic subtype, grade and hormone receptor status did not differ between the groups^6 [see Clinical Studies (14.3)].

Consistent with the WHI clinical trial, observational studies have also reported an increased risk of breast cancer with estrogen plus progestin therapy, and a smaller increase in the risk for breast cancer with estrogen-alone therapy, after several years of use. One large meta-analysis of prospective cohort studies reported increased risks that were dependent upon duration of use and could last up to >10 years after discontinuation of estrogen plus progestin therapy and estrogen-alone therapy. Extension of the WHI trials also demonstrated increased breast cancer risk associated with estrogen plus progestin therapy. Observational studies also suggest that the risk of breast cancer was greater, and became apparent earlier, with estrogen plus progestin therapy as compared to estrogen-alone therapy. These studies have not generally found significant variation in the risk of breast cancer among different estrogen plus progestin combinations, doses, or routes of administration.

The use of estrogen-alone and estrogen plus progestin has been reported to result in an increase in abnormal mammograms requiring further evaluation.

All women should receive yearly breast examinations by a healthcare provider and perform monthly breast self-examinations. In addition, mammography examinations should be scheduled based on patient age, risk factors, and prior mammogram results.

Ovarian Cancer

The CE plus MPA substudy of WHI reported that estrogen plus progestin increased the risk of ovarian cancer. After an average follow-up of 5.6 years, the relative risk for CE plus MPA versus placebo was 1.58 (95 percent CI, 0.77-3.24), but it was not statistically significant. The absolute risk for CE plus MPA versus placebo was 4 versus 3 cases per 10,000 women-years.^7

A meta-analysis of 17 prospective and 35 retrospective epidemiology studies found that women who used hormonal therapy for menopausal symptoms had an increased risk for ovarian cancer. The primary analysis, using case-control comparisons, included 12,110 cancer cases from the 17 prospective studies. The relative risks associated with current use of hormonal therapy was 1.41 (95% confidence interval [CI] 1.32 to 1.50); there was no difference in the risk estimates by duration of the exposure (less than 5 years [median of 3 years] vs. greater than 5 years [median of 10 years] of use before the cancer diagnosis). The relative risk associated with combined current and recent use (discontinued use within 5 years before cancer diagnosis) was 1.37 (95% CI 1.27 to 1.48), and the elevated risk was significant for both estrogen-alone and estrogen plus progestin products. The exact duration of hormone therapy use associated with an increased risk of ovarian cancer, however, is unknown.

5.3 Probable Dementia

In the WHI Memory Study (WHIMS) estrogen-alone ancillary study, a population of 2,947 hysterectomized women 65 to 79 years of age was randomized to daily CE (0.625 mg)-alone or placebo.

After an average follow-up of 5.2 years, 28 women in the estrogen-alone group and 19 women in the placebo group were diagnosed with probable dementia. The relative risk of probable dementia for CE-alone versus placebo was 1.49 (95 percent CI, 0.83-2.66). The absolute risk of probable dementia for CE-alone versus placebo was 37 versus 25 cases per 10,000 women-years^8 [see Use in Specific Populations (8.5), and Clinical Studies (14.4)].

In the WHIMS estrogen plus progestin ancillary study, a population of 4,532 postmenopausal women 65 to 79 years of age was randomized to daily CE (0.625 mg) plus MPA (2.5 mg) or placebo.

After an average follow-up of 4 years, 40 women in the CE plus MPA group and 21 women in the placebo group were diagnosed with probable dementia. The relative risk of probable dementia for CE plus MPA versus placebo was 2.05 (95 percent CI, 1.21-3.48). The absolute risk of probable dementia for CE plus MPA versus placebo was 45 versus 22 cases per 10,000 women-years^8 [see Use in Specific Populations (8.5), and Clinical Studies (14.4)].

When data from the two populations in the WHIMS estrogen-alone and estrogen plus progestin ancillary studies were pooled as planned in the WHIMS protocol, the reported overall relative risk for probable dementia was 1.76 (95 percent CI, 1.19-2.60). Since both ancillary studies were conducted in women 65 to 79 years of age, it is unknown whether these findings apply to younger postmenopausal women^8 [see Use in Specific Populations (8.5), and Clinical Studies (14.4)].

5.4 Gallbladder Disease

A 2- to 4-fold increase in the risk of gallbladder disease requiring surgery in postmenopausal women receiving estrogens has been reported.

5.5 Hypercalcemia

Estrogen administration may lead to severe hypercalcemia in women with breast cancer and bone metastases. Discontinue estrogens, including Climara if hypercalcemia occurs, and take appropriate measures to reduce the serum calcium level.

5.6 Visual Abnormalities

Retinal vascular thrombosis has been reported in women receiving estrogens. Discontinue Climara pending examination if there is sudden partial or complete loss of vision, or a sudden onset of proptosis, diplopia, or migraine. Permanently discontinue estrogens, including Climara, if examination reveals papilledema or retinal vascular lesions.

5.7 Addition of a Progestogen When a Woman Has Not Had a Hysterectomy

Studies of the addition of a progestogen for 10 or more days of a cycle of estrogen administration, or daily with estrogen in a continuous regimen, have reported a lowered incidence of endometrial hyperplasia than would be induced by estrogen treatment alone. Endometrial hyperplasia may be a precursor to endometrial cancer.

There are, however, possible risks that may be associated with the use of progestogens with estrogens compared to estrogen-alone regimens. These include an increased risk of breast cancer.

5.8 Elevated Blood Pressure

In a small number of case reports, substantial increases in blood pressure have been attributed to idiosyncratic reactions to estrogens. In a large, randomized, placebo-controlled clinical trial, a generalized effect of estrogens on blood pressure was not seen.

5.9 Exacerbation of Hypertriglyceridemia

In women with pre-existing hypertriglyceridemia, estrogen therapy may be associated with elevations of plasma triglycerides leading to pancreatitis. Discontinue Climara if pancreatitis occurs.

5.10 Hepatic Impairment and/or Past History of Cholestatic Jaundice

Estrogens may be poorly metabolized in women with hepatic impairment. Exercise caution in any woman with a history of cholestatic jaundice associated with past estrogen use or with pregnancy. In the case of recurrence of cholestatic jaundice, discontinue Climara.

5.11 Exacerbation of Hypothyroidism

Estrogen administration leads to increased thyroid-binding globulin (TBG) levels. Women with normal thyroid function can compensate for the increased TBG by making more thyroid hormone, thus maintaining free T4 and T3 serum concentrations in the normal range. Women dependent on thyroid hormone replacement therapy who are also receiving estrogens may require increased doses of their thyroid replacement therapy. Monitor thyroid function in these women during treatment with Climara to maintain their free thyroid hormone levels in an acceptable range.

5.12 Fluid Retention

Estrogens may cause some degree of fluid retention. Monitor any woman with a condition(s) that might predispose her to fluid retention, such as a cardiac or renal impairment. Discontinue estrogen-alone therapy, including Climara, with evidence of medically concerning fluid retention.

5.13 Hypocalcemia

Estrogen-induced hypocalcemia may occur in women with hypoparathyroidism. Consider whether the benefits of estrogen therapy, including Climara, outweigh the risks in such women.

5.14 Exacerbation of Endometriosis

A few cases of malignant transformation of residual endometrial implants have been reported in women treated post-hysterectomy with estrogen-alone therapy. Consider the addition of progestogen therapy for women known to have residual endometriosis post-hysterectomy.

5.15 Hereditary Angioedema

Exogenous estrogens may exacerbate symptoms of angioedema in women with hereditary angioedema. Consider whether the benefits of estrogen therapy, including Climara, outweigh the risks in such women.

5.16 Exacerbation of Other Conditions

Estrogen therapy, including Climara, may cause an exacerbation of asthma, diabetes mellitus, epilepsy, migraine, porphyria, systemic lupus erythematosus, and hepatic hemangiomas. Consider whether the benefits of estrogen therapy outweigh the risks in such women.

5.17 Laboratory Tests

Serum follicle stimulating hormone (FSH) and estradiol levels have not been shown to be useful in the management of postmenopausal women with moderate to severe vasomotor symptoms and moderate to severe symptoms of vulvar and vaginal atrophy.

Laboratory parameters may be useful in guiding Climara dosage for the treatment of hypoestrogenism due to hypogonadism, castration and primary ovarian failure.

5.18 Drug-Laboratory Test Interactions

Accelerated prothrombin time, partial thromboplastin time, and platelet aggregation time; increased platelet count; increased factors II, VII antigen, VIII antigen, VIII coagulant activity, IX, X, XII, VII-X complex, II-VII-X complex, and beta-thromboglobulin; decreased levels of antifactor Xa and antithrombin III, decreased antithrombin III activity; increased levels of fibrinogen and fibrinogen activity; increased plasminogen antigen and activity.

Increased TBG levels leading to increased circulating total thyroid hormone, as measured by protein-bound iodine (PBI), T4 levels (by column or by radioimmunoassay) or T3 levels by radioimmunoassay. T3 resin uptake is decreased, reflecting the elevated TBG. Free T4 and free T3 concentrations are unaltered. Women on thyroid replacement therapy may require higher doses of thyroid hormone.
Other binding proteins may be elevated in serum, for example, corticosteroid binding globulin (CBG), sex hormone-binding globulin (SHBG), leading to increased total circulating corticosteroids and sex steroids, respectively. Free hormone concentrations, such as testosterone and estradiol, may be decreased. Other plasma proteins may be increased (angiotensinogen/renin substrate, alpha-l-antitrypsin, ceruloplasmin).
Increased plasma high-density lipoprotein (HDL) and HDL2 cholesterol subfraction concentrations, reduced low-density lipoprotein (LDL) cholesterol concentration, and increased triglyceride levels.
Impaired glucose tolerance.

6 ADVERSE REACTIONS

The following serious adverse reactions are discussed elsewhere in the labeling:

- Cardiovascular Disorders [see Boxed Warning, and Warnings and Precautions (5.1)]
- Malignant Neoplasms [see Boxed Warning, and Warnings and Precautions (5.2)]

6.1 Clinical Trials Experience

Because clinical trials are conducted under widely varying conditions, adverse reaction rates observed in the clinical trials of a drug cannot be directly compared to rates in the clinical trials of another drug and may not reflect the rates observed in practice.

The data described below reflect pooled data from 5 clinical trials of Climara. A total of 614 women were exposed to Climara for 3 months (193 women at 0.025 mg per day, 201 women at 0.05 mg per day, 194 women at 0.1 mg per day) in randomized, double-blind trials of clinical efficacy versus placebo and versus active comparator. All women were postmenopausal, had a serum estradiol level of less than 20 pg/mL, and a minimum of five moderate to severe hot flushes per week or a minimum of 15 hot flushes per week of any severity at baseline. Included in this table are an additional 25 postmenopausal hysterectomized women exposed to Climara 0.025 mg per day for 6 to 24 months (N=16 at 24 months) in a randomized, double-blind, placebo-controlled study of Climara for the prevention of osteoporosis.

Table 1: Treatment-Emergent Adverse Reactions Reported at a Frequency of ≥5 Percent and More Frequent in Women Receiving Climara
 | Climara
Body System; Adverse Reactions | 0.025 mg/day [Adverse reactions occurring at rate of ≥5 percent in Climara trials of clinical efficacy versus placebo and versus active comparator; and trial of Climara versus placebo for the prevention of osteoporosis] (N=219) | 0.05 mg/day [Adverse reactions occurring at rate of ≥5 percent in Climara trials of clinical efficacy versus placebo and versus active comparator] (N=201) | 0.1 mg/day (N=194) | Placebo [Adverse reactions occurring in placebo group in Climara trial of clinical efficacy versus placebo.] (N=72)
Body as a Whole; Headache Pain Back Pain Edema | 21%; 5%; 1%; 4%; 0.5% | 39%; 18%; 8%; 8%; 13% | 37%; 13%; 11%; 9%; 10% | 29%; 10%; 7%; 6%; 6%
Digestive System; Abdominal Pain Nausea Flatulence | 9%; 0%; 1%; 1% | 21%; 11%; 5%; 3% | 29%; 16%; 6%; 7% | 18%; 8%; 3%; 1%
Musculoskeletal System; Arthralgia | 7%; 1% | 9%; 5% | 11%; 5% | 4%; 3%
Nervous System; Depression | 13%; 1% | 10%; 5% | 11%; 8% | 1%; 0%
Urogenital System; Breast Pain Leukorrhea | 12%; 5%; 1% | 18%; 8%; 6% | 41%; 29%; 7% | 11%; 4%; 1%
Respiratory System; URTI Pharyngitis Sinusitis Rhinitis | 15%; 6%; 0.5%; 4%; 2% | 26%; 17%; 3%; 4%; 4% | 29%; 17%; 7%; 5%; 6% | 14%; 8%; 3%; 3%; 1%
Skin and Appendages; Pruritus | 19%; 0.5% | 12%; 6% | 12%; 3% | 15%; 6%

6.2 Postmarketing Experience

The following adverse reactions have been identified during post-approval use of Climara. Because these reactions are reported voluntarily from a population of uncertain size, it is not always possible to reliably estimate their frequency or establish a causal relationship to drug exposure.

Genitourinary System

Changes in bleeding pattern, pelvic pain

Breast

Breast cancer, breast pain, breast tenderness

Cardiovascular

Changes in blood pressure, palpitations, hot flashes

Gastrointestinal

Vomiting, abdominal pain, abdominal distension, nausea

Skin

Alopecia, hyperhidrosis, night sweats, urticaria, rash

Eyes

Visual disturbances, contact lens intolerance,

Central Nervous System

Depression, migraine, paresthesia, dizziness, anxiety, irritability, mood swings, nervousness, insomnia, headache

Miscellaneous

Fatigue, menopausal symptoms, weight increase, application site reaction, anaphylactic reactions

7 DRUG INTERACTIONS

In vitro and in vivo studies have shown that estrogens are metabolized partially by cytochrome P450 3A4 (CYP3A4). Therefore, inducers or inhibitors of CYP3A4 may affect estrogen drug metabolism. Inducers of CYP3A4 such as St. John’s wort (hypericum perforatum) preparations, phenobarbital, carbamazepine, and rifampin may reduce plasma concentrations of estrogens, possibly resulting in a decrease in therapeutic effects and/or changes in the uterine bleeding profile. Inhibitors of CYP3A4 such as erythromycin, clarithromycin, ketoconazole, itraconazole, ritonavir and grapefruit juice may increase plasma concentrations of estrogens and may result in adverse reactions.

8 USE IN SPECIFIC POPULATIONS

8.1 Pregnancy

Risk Summary

Climara is not indicated for use in pregnancy. There are no data with the use of Climara in pregnant women; however, epidemiologic studies and meta-analyses have not found an increased risk of genital or nongenital birth defects (including cardiac anomalies and limb-reduction defects) following exposure to combined hormonal contraceptives (estrogens and progestins) before conception or during early pregnancy.

In the U.S. general population, the estimated background risk of major birth defects and miscarriage in clinically recognized pregnancies is 2% to 4% and 15% to 20%, respectively.

8.2 Lactation

Risk Summary

Estrogens are present in human milk and can reduce milk production in breast-feeding women. This reduction can occur at any time but is less likely to occur once breast-feeding is well-established. The developmental and health benefits of breastfeeding should be considered along with the mother’s clinical need for Climara and any potential adverse effects on the breastfed child from Climara or from the underlying maternal condition.

8.4 Pediatric Use

In general, Climara is not indicated for use in pediatric patients. Clinical studies have not been conducted in the pediatric population.

If estrogen is administered to patients whose bone growth is not complete, periodic monitoring of bone metabolism and effects on epiphyseal centers is recommended during estrogen administration.

8.5 Geriatric Use

There have not been sufficient numbers of geriatric women involved in clinical studies utilizing Climara to determine whether those over 65 years of age differ from younger subjects in their response to Climara.

The Women’s Health Initiative Studies

In the WHI estrogen-alone substudy (daily CE [0.625 mg]-alone versus placebo), there was a higher relative risk of stroke in women greater than 65 years of age [see Clinical Studies (14.3)].

In the WHI estrogen plus progestin substudy (daily CE [0.625 mg] plus MPA [2.5 mg] versus placebo), there was a higher relative risk of nonfatal stroke and invasive breast cancer in women greater than 65 years of age [see Clinical Studies (14.3)].

The Women’s Health Initiative Memory Study

In the WHIMS ancillary studies of postmenopausal women 65 to 79 years of age, there was an increased risk of developing probable dementia in women receiving estrogen-alone or estrogen plus progestin when compared to placebo [see Warnings and Precautions (5.3), and Clinical Studies (14.4)].

Since both ancillary studies were conducted in women 65 to 79 years of age, it is unknown whether these findings apply to younger postmenopausal women^8 [see Warnings and Precautions (5.3), and Clinical Studies (14.4)].

10 OVERDOSAGE

Overdosage of estrogen may cause nausea, vomiting, breast tenderness, abdominal pain, drowsiness and fatigue, and withdrawal bleeding in women. Treatment of overdose consists of discontinuation of Climara therapy with institution of appropriate symptomatic care.

11 DESCRIPTION

Climara (estradiol transdermal system), is designed to release estradiol continuously upon application to intact skin. Six (6.5, 9.375, 12.5, 15, 18.75 and 25 cm^2) systems are available to provide nominal in vivo delivery of 0.025, 0.0375, 0.05, 0.06, 0.075 or 0.1 mg respectively of estradiol per day. The period of use is 7 days. Each system has a contact surface area of either 6.5, 9.375, 12.5, 15, 18.75 or 25 cm^2, and contains 2, 2.85, 3.8, 4.55, 5.7 or 7.6 mg of estradiol USP respectively. The composition of the systems per unit area is identical.

Estradiol USP is a white, crystalline powder, chemically described as estra-1,3,5(10)-triene-3, 17β-diol. It has an empirical formula of C18 H24 O2 and molecular weight of 272.38. The structural formula is:

The Climara transdermal system comprises three layers. Proceeding from the visible surface toward the surface attached to the skin, these layers are:

1. A translucent polyethylene film.
2. An acrylate adhesive matrix containing estradiol USP.
3. A protective liner of siliconized or fluoropolymer-coated polyester film is attached to the adhesive surface and must be removed before the system can be used.

The active component of the transdermal system is estradiol. The remaining components of the transdermal system (acrylate copolymer adhesive, fatty acid esters, and polyethylene backing) are pharmacologically inactive.

12 CLINICAL PHARMACOLOGY

12.1 Mechanism of Action

Endogenous estrogens are largely responsible for the development and maintenance of the female reproductive system and secondary sexual characteristics. Although circulating estrogens exist in a dynamic equilibrium of metabolic interconversions, estradiol is the principal intracellular human estrogen and is substantially more potent than its metabolites, estrone and estriol at the receptor level.

The primary source of estrogen in normally cycling adult women is the ovarian follicle, which secretes 70 to 500 mcg of estradiol daily, depending on the phase of the menstrual cycle. After menopause, most endogenous estrogen is produced by conversion of androstenedione, which is secreted by the adrenal cortex, to estrone in the peripheral tissues. Thus, estrone and the sulfate conjugated form, estrone sulfate, are the most abundant circulating estrogens in postmenopausal women.

Estrogens act through binding to nuclear receptors in estrogen-responsive tissues. To date, two estrogen receptors have been identified. These vary in proportion from tissue to tissue.

Circulating estrogens modulate the pituitary secretion of the gonadotropins, luteinizing hormone (LH) and FSH, through a negative feedback mechanism. Estrogens act to reduce the elevated levels of these hormones seen in postmenopausal women.

12.2 Pharmacodynamics

Generally, a serum estrogen concentration does not predict an individual woman’s therapeutic response to Climara nor her risk for adverse outcomes. Likewise, exposure comparisons across different estrogen products to infer efficacy or safety for the individual woman may not be valid.

12.3 Pharmacokinetics

Absorption

Transdermal administration of Climara produces mean serum concentrations of estradiol comparable to those produced by premenopausal women in the early follicular phase of the ovulatory cycle. The pharmacokinetics of estradiol following application of the Climara transdermal system were investigated in 197 healthy postmenopausal women in six studies. In five of the studies, the Climara transdermal system was applied to the abdomen, and in a sixth study, application to the buttocks and abdomen were compared.

The Climara transdermal delivery system continuously releases estradiol which is transported across intact skin leading to sustained circulating levels of estradiol during a 7-day treatment period. The systemic availability of estradiol after transdermal administration is about 20 times higher than that after oral administration. This difference is due to the absence of first pass metabolism when estradiol is given by the transdermal route.

In a bioavailability study, the Climara 6.5 cm^2 was studied with the Climara 12.5 cm^2 as reference. The mean estradiol levels in serum from the two sizes are shown in Figure 1.

Figure 1: Mean Serum 17ß -Estradiol Concentrations versus Time Profile following Application of a 6.5 cm2 Transdermal System and Application of a 12.5 cm2 Climara Transdermal System

Dose proportionality was demonstrated for the Climara 6.5 cm^2 transdermal system as compared to the Climara 12.5 cm^2 transdermal system in a 2-week crossover study with a 1-week washout period between the two-transdermal systems in 24 postmenopausal women.

Dose proportionality was also demonstrated for the Climara transdermal system (12.5 cm^2 and 25 cm^2) in a 1-week study conducted in 54 postmenopausal women. The mean steady state levels (Cavg) of the estradiol during the application of Climara 25 cm^2 and 12.5 cm^2 on the abdomen were about 80 and 40 pg/mL, respectively.

In a 3-week multiple application study in 24 postmenopausal women, the 25 cm^2 Climara transdermal system produced average peak estradiol concentrations (Cmax) of approximately 100 pg/mL. Trough values at the end of each wear interval (Cmin) were approximately 35 pg/mL. Nearly identical serum curves were seen each week, indicating little or no accumulation of estradiol in the body. Serum estrone peak and trough levels were 60 and 40 pg/mL, respectively.

In a single dose, randomized, crossover study conducted to compare the effect of site of application, 38 postmenopausal women wore a single Climara 25 cm^2 transdermal system for 1 week on the abdomen and buttocks. The estradiol serum concentration profiles are shown in Figure 2. Values of Cmax and Cavg were, respectively, 25 percent and 17 percent higher with the buttock application than with the abdomen application.

Figure 2: Observed Mean (± SE) Estradiol Serum Concentrations for a One Week Application of the Climara Transdermal System (25 cm^2) to the Abdomen and Buttocks of 38 Postmenopausal Women

Table 2 provides a summary of estradiol pharmacokinetic parameters determined during evaluation of the Climara transdermal system.

Table 2: Pharmacokinetic Summary (Mean Estradiol Values)
Climara Delivery Rate | Surface Area (cm^2) | Application Site | No. of Subjects | Dosing | Cmax (pg/mL) | Cmin (pg/mL) | Cavg (pg/mL)
0.025 | 6.5 | Abdomen | 24 | Single | 32 | 17 | 22
0.05 | 12.5 | Abdomen | 102 | Single | 71 | 29 | 41
0.1 | 25 | Abdomen | 139 | Single | 147 | 60 | 87
0.1 | 25 | Buttock | 38 | Single | 174 | 71 | 106

The relative standard deviation of each pharmacokinetic parameter after application to the abdomen averaged 50 percent, which is indicative of the considerable intersubject variability associated with transdermal drug delivery. The relative standard deviation of each pharmacokinetic parameter after application to the buttock was lower than that after application to the abdomen (for example, for Cmax 39 percent versus 62 percent, and for Cavg 35 percent versus 48 percent).

Distribution

The distribution of exogenous estrogens is similar to that of endogenous estrogens. Estrogens are widely distributed in the body and are generally found in higher concentrations in the sex hormone target organs. Estrogens circulate in the blood largely bound to SHBG and albumin.

Metabolism

Exogenous estrogens are metabolized in the same manner as endogenous estrogens. Circulating estrogens exist in a dynamic equilibrium of metabolic interconversions. These transformations take place mainly in the liver. Estradiol is converted reversibly to estrone, and both can be converted to estriol, which is a major urinary metabolite. Estrogens also undergo enterohepatic recirculation via sulfate and glucuronide conjugation in the liver, biliary secretion of conjugates into the intestine, and hydrolysis in the intestine followed by reabsorption. In postmenopausal women, a significant proportion of the circulating estrogens exist as sulfate conjugates, especially estrone sulfate, which serves as a circulating reservoir for the formation of more active estrogens.

Excretion

Estradiol, estrone, and estriol are excreted in the urine along with glucuronide and sulfate conjugates.

Adhesion

An open-label study of adhesion potentials of placebo transdermal systems that correspond to the 6.5 cm^2 and 12.5 cm^2 sizes of Climara was conducted in 112 healthy women of 45 to 75 years of age. Each woman applied both transdermal systems weekly, on the upper outer abdomen, for 3 consecutive weeks. It should be noted that lower abdomen and upper quadrant of the buttock are the approved sites of application for Climara.

The adhesion assessment was done visually on Days 2, 4, 5, 6, 7 of each week of transdermal system wear. A total of 1,654 adhesion observations were conducted for 333 transdermal systems of each size.

Of these observations, approximately 90 percent showed essentially no lift for both the 6.5 cm^2 and 12.5 cm^2 transdermal systems. Of the total number of transdermal systems applied, approximately 5 percent showed complete detachment for each size. Adhesion potentials of the 18.75 cm^2 and 25 cm^2 sizes of transdermal systems (0.075 mg per day and 0.1 mg per day) have not been studied.

13 NONCLINICAL TOXICOLOGY

13.1 Carcinogenesis, Mutagenesis, Impairment of Fertility

Long-term continuous administration of natural and synthetic estrogens in certain animal species increases the frequency of carcinomas of the breast, uterus, cervix, vagina, testis, and liver.

14 CLINICAL STUDIES

14.1 Effects on Vasomotor Symptoms in Postmenopausal Women

A study of 214 women 25 to 74 years of age met the qualification criteria and were randomly assigned to one of the three treatment groups: 72 to the 0.05 mg estradiol patch, 70 to the 0.1 mg estradiol patch, and 72 to placebo. Potential participants were postmenopausal women in good general health who experienced vasomotor symptoms. Natural menopause patients had not menstruated for at least 12 months and surgical menopause patients had undergone bilateral oophorectomy at least 4 weeks before evaluation for study entry. In order to enter the 11-week treatment phase of the study, potential participants must have experienced a minimum of five moderate to severe hot flushes per week, or a minimum of 15 hot flushes of any severity per week, for 2 consecutive weeks. Women wore the patches in a cyclical fashion (three weeks on and one week off).

During treatment, all women used diaries to record the number and severity of hot flushes. Women were monitored by clinic visits at the end of weeks 1, 3, 7, and 11 and by telephone at the end of weeks 4, 5, 8, and 9.

Adequate data for the analysis of efficacy was available from 191 subjects. The results are presented as the mean ± SD number of flushes in each of the 3 treatment weeks of each 4-week cycle. In the 0.05 mg estradiol group, the mean weekly hot flush rate across all treatment cycles decreased from 46 ± 6.5 at baseline to 20 ± 3 (-67 percent). The 0.1 mg estradiol group had a decline in the mean weekly hot flush rate from 52 ± 4.4 at baseline to 16 ± 2.4 (-72 percent). In the placebo group, the mean weekly hot flush rate declined from 53 ± 4.5 at baseline to 46 ± 6.5 (-18.1 percent). Compared with placebo, the 0.05 mg and 0.1 mg estradiol groups showed a statistically significantly larger mean decrease in hot flushes across all treatment cycles (P<0.05). When the response to treatment was analyzed for each of the three cycles of therapy, similar statistically significant differences were observed between both estradiol treatment groups and the placebo group during all treatment cycles.

In a double-blind, placebo-controlled, randomized study of 187 women receiving Climara 0.025 mg per day or placebo continuously for up to three 28-day cycles, the Climara 0.025 mg per day dosage was shown to be statistically better than placebo at weeks 4 and 12 for relief of both the frequency and severity of moderate to severe vasomotor symptoms.

Table 3: Mean Change from Baseline in the Number of Moderate to Severe Vasomotor Symptoms Intent to Treat (ITT)
Treatment Group | Statistics | Week 4 | Week 8 | Week 12
E2 Transdermal System | N | 82 | 84 | 68
 | Mean | -6.45 | -7.69 | -7.56
 | SD | 4.65 | 4.76 | 4.64
Placebo | N | 83 | 71 | 65
Placebo | Mean | -5.11 | -5.98 | -5.98
Placebo | SD | 7.43 | 8.63 | 9.69
Placebo | p-value | <0.002 |  | <0.003

A second active-control trial of 193 randomized women was supportive of the placebo-controlled trial.

14.2 Effects on Bone Mineral Density in Postmenopausal Women

A two-year clinical trial enrolled a total of 175 healthy, hysterectomized, postmenopausal, non-osteoporotic (that is, lumbar spine bone mineral density >0.9 gm/cm^2) women at 10 study centers in the United States. A total of 129 participating women were allocated to receive active treatment with 4 different doses of estradiol patches (6.5, 12.5, 15, 25 cm^2) and 46 participating women were allocated to receive placebo patches. Seventy-seven percent of the randomized women (100 on active drug and 34 on placebo) contributed data to the analysis of percent change of anterior-posterior (A-P) spine BMD, the primary efficacy variable (see Figure 3). A statistically significant overall treatment effect at each timepoint was noted, implying bone preservation for all active treatment groups at all timepoints, as opposed to bone loss for placebo at all timepoints.

Figure 3: Mean Percent Change from Baseline in Lumbar Spine (A-P View) Bone Mineral Density By Treatment and Time Last Observation Carried Forward

Figure 3: Mean Percent Change from Baseline in Lumbar Spine (A-P View) Bone Mineral Density By Treatment and Time Last Observation Carried Forward

Percent change in BMD of the total hip (see Figure 4) was also statistically significantly different from placebo for all active treatment groups. This figure is based on 74 percent of the randomized women (95 on active drug and 34 on placebo).

Figure 4: Mean Percent Change from Baseline in Total Hip by Treatment and Time Last Observation Carried Forward

14.3 Women's Health Initiative Studies

The WHI enrolled approximately 27,000 predominantly healthy postmenopausal women in two substudies to assess the risks and benefits of daily oral CE (0.625 mg)-alone or in combination with MPA (2.5 mg) compared to placebo in the prevention of certain chronic diseases. The primary endpoint was the incidence of CHD (defined as nonfatal MI, silent MI and CHD death), with invasive breast cancer as the primary adverse outcome. A "global index" included the earliest occurrence of CHD, invasive breast cancer, stroke, PE, endometrial cancer (only in the CE plus MPA substudy), colorectal cancer, hip fracture, or death due to other causes. These substudies did not evaluate the effects of CE-alone or CE plus MPA on menopausal symptoms.

WHI Estrogen-Alone Substudy

The WHI estrogen-alone substudy was stopped early because an increased risk of stroke was observed, and it was deemed that no further information would be obtained regarding the risk and benefits of estrogen-alone in predetermined primary endpoints.

Results of the estrogen-alone substudy, which included 10,739 women (average 63 years of age, range 50 to 79: 75.3 percent White, 15.1 percent Black, 6.1 percent Hispanic, 3.6 percent Other) after an average follow-up of 7.1 years, are presented in Table 4.

Table 4: Relative and Absolute Risk Seen in the Estrogen-Alone Substudy of WHI [Adapted from numerous WHI publications. WHI publications can be viewed at www.nhlbi.nih.gov/whi]
Event | Relative Risk CE vs. Placebo (95% nCI [Nominal confidence intervals unadjusted for multiple looks and multiple comparisons.]) | CE n = 5,310 | Placebo n = 5,429
Event | Relative Risk CE vs. Placebo (95% nCI [Nominal confidence intervals unadjusted for multiple looks and multiple comparisons.]) | Absolute Risk per 10,000 Women-years
CHD events | 0.95 (0.78-1.16) | 54 | 57
Non-fatal MIc | 0.91 (0.73-1.14) | 40 | 43
CHD death [Results are based on centrally adjudicated data for an average follow-up of 7.1 years.] | 1.01 (0.71-1.43) | 16 | 16
All strokes | 1.33 (1.05-1.68) | 45 | 33
Ischemic stroke | 1.55 (1.19-2.01) | 38 | 25
Deep vein thrombosis, [Not included in "global index".] | 1.47 (1.06-2.06) | 23 | 15
Pulmonary embolism | 1.37 (0.9-2.07) | 14 | 10
Invasive breast cancer | 0.80 (0.62-1.04) | 28 | 34
Colorectal cancer | 1.08 (0.75-1.55) | 17 | 16
Hip fracture | 0.65 (0.45-0.94) | 12 | 19
Vertebral fractures, | 0.64 (0.44-0.93) | 11 | 18
Lower arm/wrist fractures, | 0.58 (0.47-0.72) | 35 | 59
Total fractures, | 0.71 (0.64-0.80) | 144 | 197
Death due to causes [Results are based on an average follow-up of 6.8 years.] , [All deaths, except from breast or colorectal cancer, definite or probable CHD, PE or cerebrovascular disease.] | 1.08 (0.88-1.32) | 53 | 50
Overall mortality, | 1.04 (0.88-1.22) | 79 | 75
Global Index [A subset of the events was combined in a "global index", defined as the earliest occurrence of CHD events, invasive breast cancer, stroke, pulmonary embolism, endometrial cancer, colorectal cancer, hip fracture, or death due to other causes.] | 1.02 (0.92-1.13) | 206 | 201

For those outcomes included in the WHI "global index" that reached statistical significance, the absolute excess risks per 10,000 women-years in the group treated with CE-alone was 12 more strokes, while the absolute risk reduction per 10,000 women-years was 7 fewer hip fractures.^9 The absolute excess risk of events included in the "global index" was a non-significant 5 events per 10,000 women-years. There was no difference between the groups in terms of all-cause mortality.

No overall difference for primary CHD events (nonfatal MI, silent MI and CHD death) and invasive breast cancer incidence in women receiving CE-alone compared with placebo was reported in final centrally adjudicated results from the estrogen-alone substudy, after an average follow-up of 7.1 years. See Table 4.

Centrally adjudicated results for stroke events from the estrogen-alone substudy, after an average follow-up of 7.1 years, reported no significant difference in the distribution of stroke subtype and severity, including fatal strokes, in women receiving estrogen-alone compared to placebo. Estrogen-alone increased the risk of ischemic stroke, and this excess risk was present in all subgroups of women examined.^10 See Table 4.

Timing of initiation of estrogen-alone therapy relative to the start of menopause may affect the overall risk-benefit profile. The WHI estrogen-alone substudy stratified by age showed in women 50 to 59 years of age a non-significant trend toward reduced risk for CHD [hazard ratio (HR) 0.63 (95 percent CI, 0.36-1.09)] and overall mortality [HR 0.71 (95 percent CI, 0.46-1.11)].

WHI Estrogen Plus Progestin Substudy

The WHI estrogen plus progestin substudy was stopped early. According to the predefined stopping rule, after an average follow-up of 5.6 years of treatment, the increased risk of invasive breast cancer and cardiovascular events exceeded the specified benefits included in the "global index". The absolute excess risk of events included in the “global index” was 19 per 10,000 women-years.

For those outcomes included in the WHI “global index” that reached statistical significance after 5.6 years of follow-up, the absolute excess risks per 10,000 women-years in the group treated with CE plus MPA were 7 more CHD events, 8 more strokes, 10 more PEs, and 8 more invasive breast cancers, while the absolute risk reduction per 10,000 women-years were 6 fewer colorectal cancers and 5 fewer hip fractures.

Results of the CE plus MPA substudy, which included 16,608 women (average 63 years of age, range 50 to 79; 83.9 percent White, 6.5 percent Black, 5.4 percent Hispanic, 3.9 percent Other), are presented in Table 5 . These results reflect centrally adjudicated data after an average follow-up of 5.6 years.

Table 5: Relative and Absolute Risk Seen in the Estrogen Plus Progestin Substudy of WHI at an Average of 5.6 Years
Event | Relative Risk CE/MPA vs. placebo (95% nCI [Nominal confidence intervals unadjusted for multiple looks and multiple comparisons.]) | CE/MPA n = 8,506 | Placebo; n = 8,102
Event |  | Absolute Risk per 10,000 Women-years
CHD events | 1.23 (0.99-1.53) | 41 | 34
Non-fatal MI | 1.28 (1.00-1.63) | 31 | 25
CHD death | 1.10 (0.70-1.75) | 8 | 8
All strokes | 1.31 (1.03-1.68) | 33 | 25
Ischemic stroke | 1.44 (1.09-1.90) | 26 | 18
Deep vein thrombosis [Not included in "global index".] | 1.95 (1.43-2.67) | 26 | 13
Pulmonary embolism | 2.13 (1.45-3.11) | 18 | 8
Invasive breast cancer [Includes metastatic and non-metastatic breast cancer, with the exception of in situ breast cancer.] | 1.24 (1.01-1.54) | 41 | 33
Colorectal cancer | 0.61 (0.42-0.87) | 10 | 16
Endometrial cancer | 0.81 (0.48-1.36) | 6 | 7
Cervical cancer | 1.44 (0.47-4.42) | 2 | 1
Hip fracture | 0.67 (0.47-0.96) | 11 | 16
Vertebral fractures | 0.65 (0.46-0.92) | 11 | 17
Lower arm/wrist fractures | 0.71 (0.59-0.85) | 44 | 62
Total fractures | 0.76 (0.69-0.83) | 152 | 199
Overall mortality [All deaths, except from breast or colorectal cancer, definite or probable CHD, PE or cerebrovascular disease.] | 1.00 (0.83-1.19) | 52 | 52
Global Index [A subset of the events was combined in a "global index", defined as the earliest occurrence of CHD events, invasive breast cancer, stroke, pulmonary embolism, endometrial cancer, colorectal cancer, hip fracture, or death due to other causes.] | 1.13 (1.02-1.25) | 184 | 165
Adapted from numerous WHI publications. WHI publications can be viewed at www.nhlbi.nih.gov/whi. Results are based on centrally adjudicated data.

Timing of initiation of estrogen plus progestin therapy relative to the start of menopause may affect the overall risk benefit profile. The WHI estrogen plus progestin substudy stratified by age showed in women 50 to 59 years of age a non-significant trend toward reduced risk for overall mortality [HR 0.69 (95 percent CI, 0.44-1.07)].

14.4 Women's Health Initiative Memory Study

The WHIMS estrogen-alone ancillary study of WHI enrolled 2,947 predominantly healthy hysterectomized postmenopausal women 65 to 79 years of age and older (45 percent were 65 to 69 years of age; 36 percent were 70 to 74 years of age; 19 percent were 75 years of age and older) to evaluate the effects of daily CE (0.625 mg)-alone on the incidence of probable dementia (primary outcome) compared to placebo.

After an average follow-up of 5.2 years, the relative risk of probable dementia for CE-alone versus placebo was 1.49 (95 percent CI, 0.83-2.66). The absolute risk of probable dementia for CE-alone versus placebo was 37 versus 25 cases per 10,000 women-years. Probable dementia as defined in the study included Alzheimer’s disease (AD), vascular dementia (VaD) and mixed types (having features of both AD and VaD). The most common classification of probable dementia in the treatment group and the placebo group was AD. Since the ancillary study was conducted in women 65 to 79 years of age, it is unknown whether these findings apply to younger postmenopausal women [see Warnings and Precautions (5.3), and Use in Specific Populations (8.5)].

The WHIMS estrogen plus progestin ancillary study enrolled 4,532 predominantly healthy postmenopausal women 65 years of age and older (47 percent were 65 to 69 years of age; 35 percent were 70 to 74 years of age; and 18 percent were 75 years of age and older) to evaluate the effects of daily CE (0.625 mg) plus MPA (2.5 mg) on the incidence of probable dementia (primary outcome) compared to placebo.

After an average follow-up of 4 years, the relative risk of probable dementia for CE plus MPA versus placebo was 2.05 (95 percent CI, 1.21-3.48). The absolute risk of probable dementia for CE plus MPA versus placebo was 45 versus 22 cases per 10,000 women-years. Probable dementia as defined in the study included AD, VaD and mixed types (having features of both AD and VaD). The most common classification of probable dementia in the treatment group and the placebo group was AD. Since the ancillary study was conducted in women 65 to 79 years of age, it is unknown whether these findings apply to younger postmenopausal women [see Warnings and Precautions (5.3), and Use in Specific Populations (8.5)].

When data from the two populations were pooled as planned in the WHIMS protocol, the reported overall relative risk for probable dementia was 1.76 (95 percent CI, 1.19-2.60). Differences between groups became apparent in the first year of treatment. It is unknown whether these findings apply to younger postmenopausal women [see Warnings and Precautions (5.3), and Use in Specific Populations (8.5)]

15 REFERENCES

1. Rossouw JE, et al. Postmenopausal Hormone Therapy and Risk of Cardiovascular Disease by Age and Years Since Menopause. JAMA. 2007;297:1465-1477.
2. Hsia J, et al. Conjugated Equine Estrogens and Coronary Heart Disease. Arch Int Med. 2006;166:357-365.
3. Curb JD, et al. Venous Thrombosis and Conjugated Equine Estrogen in Women Without a Uterus. Arch Int Med. 2006;166:772-780.
4. Cushman M, et al. Estrogen Plus Progestin and Risk of Venous Thrombosis. JAMA. 2004;292:1573-1580.
5. Stefanick ML, et al. Effects of Conjugated Equine Estrogens on Breast Cancer and Mammography Screening in Postmenopausal Women With Hysterectomy. JAMA. 2006;295:1647-1657.
6. Chlebowski RT, et al. Influence of Estrogen Plus Progestin on Breast Cancer and Mammography in Healthy Postmenopausal Women. JAMA. 2003;289:3234-3253.
7. Anderson GL, et al. Effects of Estrogen Plus Progestin on Gynecologic Cancers and Associated Diagnostic Procedures. JAMA. 2003;290:1739-1748.
8. Shumaker SA, et al. Conjugated Equine Estrogens and Incidence of Probable Dementia and Mild Cognitive Impairment in Postmenopausal Women. JAMA. 2004;291:2947-2958.
9. Jackson RD, et al. Effects of Conjugated Equine Estrogen on Risk of Fractures and BMD in Postmenopausal Women With Hysterectomy: Results From the Women's Health Initiative Randomized Trial. J Bone Miner Res. 2006;21:817-828.
10. Hendrix SL, et al. Effects of Conjugated Equine Estrogen on Stroke in the Women's Health Initiative. Circulation. 2006;113:2425-2434.

16 HOW SUPPLIED/STORAGE AND HANDLING

16.1 How Supplied

Climara (estradiol transdermal system), 0.025 mg per day — each 6.5 cm^2 system contains 2 mg of estradiol USP
Individual Carton of 4 systems NDC 50419-454-04

Climara (estradiol transdermal system), 0.0375 mg per day — each 9.375 cm^2 system contains 2.85 mg of estradiol USP
Individual Carton of 4 systems NDC 50419-456-04

Climara (estradiol transdermal system), 0.05 mg per day — each 12.5 cm^2 system contains 3.8 mg of estradiol USP
Individual Carton of 4 systems NDC 50419-451-04

Climara (estradiol transdermal system), 0.06 mg per day — each 15 cm^2 system contains 4.55 mg of estradiol USP
Individual Carton of 4 systems NDC 50419-459-04

Climara (estradiol transdermal system), 0.075 mg per day — each 18.75 cm^2 system contains 5.7 mg of estradiol USP
Individual Carton of 4 systems NDC 50419-453-04

Climara (estradiol transdermal system), 0.1 mg per day — each 25 cm^2 system contains 7.6 mg of estradiol USP
Individual Carton of 4 systems NDC 50419-452-04

16.2 Storage and Handling

Store at 20°C to 25°C (66°F to 77°F); excursions permitted between 15°C and 30°C (59°F and 86°F). Do not store above 86°F (30°C).

Do not store unpouched. Apply immediately upon removal from the protective pouch.

Used transdermal systems still contain active hormone. To discard, fold the sticky side of the transdermal system together, place it in a sturdy child-proof container, and place this container in the trash. Used transdermal systems should not be flushed in the toilet.

17 PATIENT COUNSELING INFORMATION

Advise women to read the FDA-approved patient labeling (Patient Information and Instructions for Use)

Vaginal Bleeding

Inform postmenopausal women to report any vaginal bleeding to their healthcare provider as soon as possible [see Warning and Precautions (5.2)].

Possible Serious Adverse Reactions with Estrogen-Alone Therapy

Inform postmenopausal women of possible serious adverse reactions of estrogen-alone therapy including Cardiovascular Disorders, Malignant Neoplasms, and Probable Dementia [see Warnings and Precautions (5.1, 5.2, 5.3)].

Possible Common Adverse Reactions with Estrogen-Alone Therapy

Inform postmenopausal women of possible less serious but common adverse reactions of estrogen-alone therapy such as headache, breast pain and tenderness, nausea and vomiting.

Patient Package Insert

Patient Information

Climara (Klī-mâr-uh)

(estradiol transdermal system)

Read this Patient Information before you start using Climara and each time you get a refill. There may be new information. This information does not take the place of talking to your healthcare provider about your menopausal symptoms or your treatment.

What is the most important information I should know about Climara (an estrogen hormone)?

- Using estrogen-alone may increase your chance of getting cancer of the uterus (womb).
- Report any unusual vaginal bleeding right away while you are using Climara. Vaginal bleeding after menopause may be a warning sign of cancer of the uterus (womb). Your healthcare provider should check any unusual vaginal bleeding to find out the cause.
- Do not use estrogen-alone to prevent heart disease, heart attacks, strokes, or dementia (decline in brain function).
- Using estrogen-alone may increase your chances of getting strokes or blood clots.
- Using estrogen-alone may increase your chance of getting dementia, based on a study of women age 65 years of age and older.
- Do not use estrogens with progestogens to prevent heart disease, heart attacks, strokes or dementia.
- Using estrogens with progestogens may increase your chances of getting heart attacks, strokes, breast cancer, or blood clots.
- Using estrogens with progestogens may increase your chance of getting dementia, based on a study of women age 65 years of age and older.
- Only one estrogen-alone product and dose have been shown to increase your chances of getting strokes, blood clots, and dementia. Only one estrogen with progestogen product and dose have been shown to increase your chances of getting heart attacks, strokes, breast cancer, blood clots, and dementia.
- Because other products and doses have not been studied in the same way, it is not known how the use of Climara will affect your chances of these conditions. You and your healthcare provider should talk regularly about whether you still need treatment with Climara.

What is Climara?

Climara is a prescription medicine patch (transdermal system) that contains estradiol (an estrogen hormone).

What is Climara used for?

The Climara is used after menopause to:

- Reduce moderate to severe hot flashes
Estrogens are hormones made by a woman’s ovaries. The ovaries normally stop making estrogens when a woman is between 45 and 55 years old. This drop in body estrogen levels causes the "change of life" or menopause (the end of monthly menstrual periods). Sometimes, both ovaries are removed during an operation before natural menopause takes place. The sudden drop in estrogen levels causes "surgical menopause."
When estrogen levels begin dropping, some women develop very uncomfortable symptoms, such as feelings of warmth in the face, neck, and chest, or sudden intense feelings of heat and sweating ("hot flashes" or "hot flushes"). In some women, the symptoms are mild, and they will not need to use estrogens. In other women, symptoms can be more severe.
- Treat moderate to severe menopausal changes in and around the vagina
You and your healthcare provider should talk regularly about whether you still need treatment with Climara to control these problems. If you use Climara only to treat your menopausal changes in and around your vagina, talk with your healthcare provider about whether a topical vaginal product would be better for you.
- Treat certain conditions in women before menopause if their ovaries do not produce enough estrogens naturally
- Help reduce your chances of getting osteoporosis (thin weak bones)
Osteoporosis from menopause is a thinning of the bones that makes them weaker and easier to break. If you use Climara only to prevent osteoporosis due to menopause, talk with your healthcare provider about whether a different treatment or medicine without estrogens might be better for you.

You and your healthcare provider should talk regularly about whether you still need treatment with Climara.

Who should not use Climara?

Do not start using Climara if you:

- have unusual vaginal bleeding
Vaginal bleeding after menopause may be a warning sign of cancer of the uterus (womb). Your healthcare provider should check any unusual vaginal bleeding to find out the cause.
- have been diagnosed with a bleeding disorder
- currently have or have had certain cancers
Estrogens may increase the chance of getting certain types of cancers, including cancer of the breast or uterus (womb). If you have or have had cancer, talk with your healthcare provider about whether you should use Climara.
- had a stroke or heart attack
- currently have or have had blood clots
- currently have or have had liver problems
- are allergic to Climara or any of the ingredients in it. See the list of ingredients in Climara at the end of this leaflet.

Before you use Climara, tell your healthcare provider about all of your medical conditions, including if you:

- have any unusual vaginal bleeding
Vaginal bleeding after menopause may be a warning sign of cancer of the uterus (womb). Your healthcare provider should check any unusual vaginal bleeding to find out the cause.
- have any other medical conditions that may become worse while you are using Climara
Your healthcare provider may need to check you more carefully if you have certain conditions, such as asthma (wheezing), epilepsy (seizures), diabetes, migraine, endometriosis, lupus, angioedema (swelling of face and tongue), or problems with your heart, liver, thyroid, kidneys, or have high calcium levels in your blood.
- are going to have surgery or will be on bed rest.
Your healthcare provider will let you know if you need to stop using Climara.
- are pregnant or think you may be pregnant.
Climara is not for pregnant women.

- are breastfeeding
The hormone in Climara can pass into your breast milk.

Tell your healthcare provider about all the medicines you take, including prescription and over-the-counter medicines, vitamins, and herbal supplements. Some medicines may affect how Climara works. Climara may also affect how your other medicines work. Keep a list of your medicines and show it to your healthcare provider and pharmacist when you get new medicine.

How should I use Climara?

For detailed instructions, see the step-by-step instructions for using Climara at the end of this Patient Information.

- Use Climara exactly as your healthcare provider tells you to use it.
- Climara is for skin use only.
- Change your Climara patch 1 time each week or every 7 days.
- Apply your Climara patch to a clean, dry area on your lower abdomen or buttocks. This area must be clean, dry, and free of powder, oil or lotion for your patch to stick to your skin.
- Apply your Climara patch to a different area of your abdomen or your buttocks each time. Do not use the same application site 2 times in the same week.
- Do not apply Climara to your breasts.
- If you forget to apply a new Climara patch, apply a new patch as soon as possible.
- You and your healthcare provider should talk regularly (every 3 to 6 months) about the dose you are using and whether you still need treatment with Climara.

How to Change Climara

- When changing Climara, peel off the used patch slowly from the skin.
- After removal of Climara if any adhesive residue remains on your skin, allow the area to dry for 15 minutes. Then, gently rub the area with an oil-based cream or lotion to remove the adhesive from your skin.
- Apply the new patch to a different area of your abdomen or buttocks. This area must be clean, dry, and free of powder, oil or lotion. Do not use the same site again for at least 1 week after removal of an old patch.

What are the possible side effects of Climara?

Side effects are grouped by how serious they are and how often they happen when you are treated.

Serious, but less common side effects include:

Call your healthcare provider right away if you get any of the following warning signs or any other unusual symptoms that concern you:

- new breast lumps
- unusual vaginal bleeding
- changes in vision or speech
- sudden new severe headaches
- severe pains in your chest or legs with or without shortness of breath, weakness and fatigue

Common side effects of Climara include:

- headache
- breast tenderness or pain
- irregular vaginal bleeding or spotting
- stomach or abdominal cramps, bloating
- nausea and vomiting
- hair loss
- fluid retention
- vaginal yeast infection
- redness and/or irritation at the patch placement site

These are not all the possible side effects of Climara. For more information, ask your healthcare provider or pharmacist. Tell your healthcare provider if you have any side effects that bother you or do not go away.

You may report side effects to FDA at 1-800-FDA-1088. You may report side effects to Bayer Healthcare Pharmaceuticals at 1-888-842-2937.

What can I do to lower my chances of a serious side effect with Climara?

- Talk with your healthcare provider regularly about whether you should continue using Climara.
- If you have a uterus, talk with your healthcare provider about whether the addition of a progestogen is right for you. In general, the addition of a progestogen is generally recommended for a woman with a uterus to reduce the chance of getting cancer of the uterus (womb).
- See your healthcare provider right away if you get vaginal bleeding while using Climara.
- Have a pelvic exam, breast exam and mammogram (breast X-ray) every year unless your healthcare provider tells you something else. If members of your family have had breast cancer or if you have ever had breast lumps or an abnormal mammogram, you may need to have breast exams more often.
- If you have high blood pressure, high cholesterol (fat in the blood), diabetes, are overweight, or if you use tobacco, you may have higher chances for getting heart disease. Ask your healthcare provider for ways to lower your chances of getting heart disease.

How should I store and throw away used Climara?

- Store Climara at room temperature 68°F to 77°F (20°C to 25°C).
- Do not store Climara patches outside of their pouches. Apply immediately upon removal from the protective pouch.
- Used patches still contain estrogen. To throw away the patch, fold the sticky side of the patch together, place it in a sturdy child-proof container, and place this container in the trash. Used patches should not be flushed in the toilet.

Keep Climara and all medicines out of the reach of children.

General information about the safe and effective use of Climara.

Medicines are sometimes prescribed for purposes other than those listed in Patient Information leaflets. Do not use Climara for conditions for which it was not prescribed. Do not give Climara to other people, even if they have the same symptoms you have. It may harm them.

You can ask your healthcare provider or pharmacist for information about Climara that is written for health professionals. For more information, go to www.climara.com or call Bayer HealthCare Pharmaceuticals Inc at 1-888-842-2937.

What are the ingredients in Climara?

Active ingredient: estradiol

Inactive ingredient: acrylate copolymer adhesive, fatty acid esters, and polyethylene backing.

INSTRUCTIONS FOR USE

Climara (Klī-mâr-uh)

(estradiol transdermal system)

Read this Patient Information before you start using Climara and each time you get a refill. There may be new information. This information does not take the place of talking to your healthcare provider about your menopausal symptoms or your treatment.

You will need the following supplies: See Figure A

Figure A

Step 1: Pick the days you will change your Climara.

You will need to change your patch 1 time each week or every 7 days.

Step 2. Remove the Climara patch from the pouch.

- Remove patch from its protective pouch by tearing at the notch (do not use scissors). See Figure B
- Do not remove your patch from the protective pouch until you are ready to apply it.

Figure B

Step 3. Remove the adhesive liner. See Figure C

- You will see that Climara is an oval shaped clear patch that is attached to a thick, hard-plastic adhesive liner and covered by a clear, plastic film. See Figure C
- To apply your patch you must first remove the protective, clear plastic film that is attached to the clear thicker plastic backing. See Figure D
- There is a silver foil-sticker attached to the inside of the pouch. Do not remove the silver foil sticker from the pouch. See Figure E

Figure C

Figure D

Figure E

Step 4. Placing the patch on your skin.

- Apply the sticky side of the patch to 1 of the areas of skin shown below. See Figure F and Figure G
- Do not touch the sticky side of the patch with your fingers.

Figure F

Figure G

Note:

- Avoid the waistline, since clothing and belts may cause the patch to be rubbed off.
- Do not apply Climara to your breasts.
- Only apply Climara to skin that is clean, dry, and free of any powder, oil, or lotion.
- Do not apply the patch to injured, burned, or irritated skin, or areas with skin conditions (such as birth marks, tattoos, or that is very hairy).

Step 5. Press the patch firmly onto your skin.

- Press the patch firmly in place with your fingers for at least 10 seconds
- Rub the edges of the patch to make sure that it will stick to your skin. (See Figure H)

Figure H

Note:

- Contact with water while you are swimming, using a sauna, bathing, or showering may cause the patch to fall off.
- If your patch falls off reapply it. If you cannot reapply the patch, apply a new patch to another area (See Figures F and G), and continue to follow your original application schedule.
- If you stop using your Climara patch or forget to apply a new patch as scheduled, you may have spotting, or bleeding, and your symptoms may come back.

Step 6: Throwing away your used patch.

- When it is time to change your patch, remove the old patch before you apply a new patch.
- To throw away the patch, fold the sticky side of the patch together, place it in a sturdy child-proof container, and place this container in the trash. Do not flush used patches in the toilet.

This Patient Information and Instructions for Use have been approved by the U.S Food and Drug Administration.

Revised 9/2021

© 2013, Bayer HealthCare Pharmaceuticals Inc. All rights reserved.

Manufactured for:

Bayer HealthCare Pharmaceuticals Inc.
Whippany, NJ 07981

PACKAGE/LABEL PRINCIPAL DISPLAY PANEL

NDC 50419-454-04

4 transdermal systems

Climara®

(estradiol transdermal system)

0.025 mg/day

Contents: Each 6.5 cm^2 system contains 2 mg estradiol USP to
provide 0.025 mg of estradiol per day. The inactive components
are acrylate copolymer adhesive, fatty acid esters, and
polyethylene backing.

For transdermal use only.

Keep this and all drugs out of the reach of children.

PACKAGE/LABEL PRINCIPAL DISPLAY PANEL

Climara®

(estradiol transdermal system)

0.0375 mg/day

Contents: Each 9.375 cm^2 system contains 2.85 mg estradiol USP to
provide 0.0375 mg of estradiol per day. The inactive components
are acrylate copolymer adhesive, fatty acid esters, and
polyethylene backing.

For transdermal use only.

Keep this and all drugs out of the reach of children.

Rx only

PACKAGE/LABEL PRINCIPAL DISPLAY PANEL

Climara®

(estradiol transdermal system)

0.05 mg/day

Contents: Each 12.5 cm^2 system contains 3.8 mg estradiol USP to
provide 0.05 mg of estradiol per day. The inactive components
are acrylate copolymer adhesive, fatty acid esters, and
polyethylene backing.

For transdermal use only.

Keep this and all drugs out of the reach of children.

Rx only

PACKAGE/LABEL PRINCIPAL DISPLAY PANEL

Climara®

(estradiol transdermal system)

0.06 mg/day

Contents: Each 15 cm^2 system contains 4.55 mg estradiol USP to
provide 0.06 mg of estradiol per day. The inactive components
are acrylate copolymer adhesive, fatty acid esters, and
polyethylene backing.

For transdermal use only.

Keep this and all drugs out of the reach of children.

Rx only

PACKAGE/LABEL PRINCIPAL DISPLAY PANEL

Climara®

(estradiol transdermal system)

0.075 mg/day

Contents: Each 18.75 cm^2 system contains 5.7 mg estradiol USP to
provide 0.075 mg of estradiol per day. The inactive components
are acrylate copolymer adhesive, fatty acid esters, and
polyethylene backing.

For transdermal use only.

Keep this and all drugs out of the reach of children.

Rx only

PACKAGE/LABEL PRINCIPAL DISPLAY PANEL

Climara®

(estradiol transdermal system)

0.1 mg/day

Contents: Each 25 cm^2 system contains 7.6 mg estradiol USP to
provide 0.1 mg of estradiol per day. The inactive components
are acrylate copolymer adhesive, fatty acid esters, and
polyethylene backing.

For transdermal use only.

Keep this and all drugs out of the reach of children.

Rx only